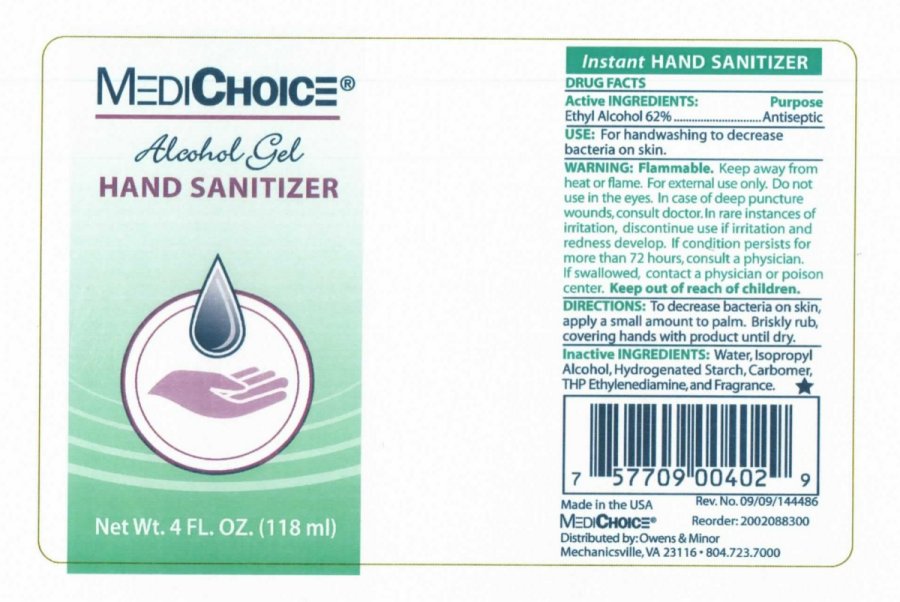 DRUG LABEL: MediChoice Hand Sanitizer
NDC: 55504-4000 | Form: GEL
Manufacturer: Donovan Industries, Inc.
Category: otc | Type: HUMAN OTC DRUG LABEL
Date: 20091210

ACTIVE INGREDIENTS: ALCOHOL 62 mL/100 mL
INACTIVE INGREDIENTS: WATER; ISOPROPYL ALCOHOL; CARBOMER HOMOPOLYMER TYPE C; ETHYLENEDIAMINE

MediChoice Alcohol Gel Hand Sanitizer

Drug Facts

Active Ingredients: Purpose

Ethyl Alcohol 62 percent Antiseptic

PURPOSE

Use: For handwashing to decrease bacteria on skin.

Warnings:

Flammable. Keep away from heat or flame.

For external use only.

Do not use in the eyes.

In case of deep or puncture wounds, consult doctor.

In rare instances of irritation, discontinue use if irritation and redness develop.

If condition persists for more than 72 hours, consult a physician.

If swallowed, contact a physician or poison center.

Keep out of reach of children.

Directions:

To decrease bacteria on skin, apply a small amount to palm.

Briskly rub covering hands with product until dry.

INACTIVE INGREDIENT

Inactive Ingredients: Water, Isopropyl Alcohol, Hydrogenated Starch, Carbomer, THP Ethylenediamine, and Fragrance.

PACKAGE LABEL

MediChoice

Alcohol Gel

Hand Sanitizer

4 FL. OZ. 118ml